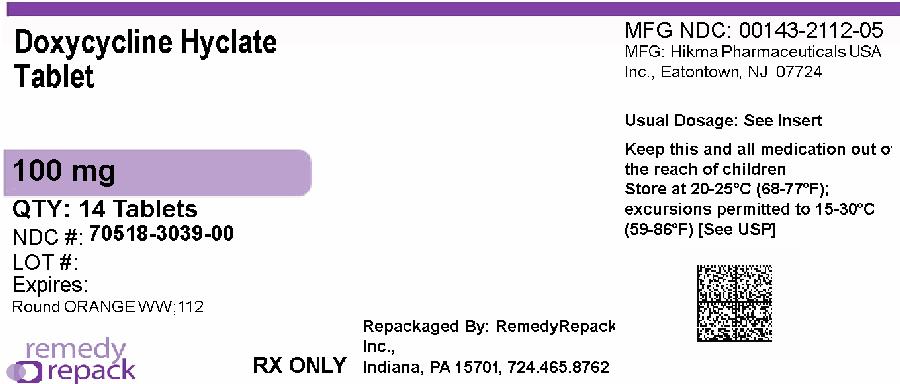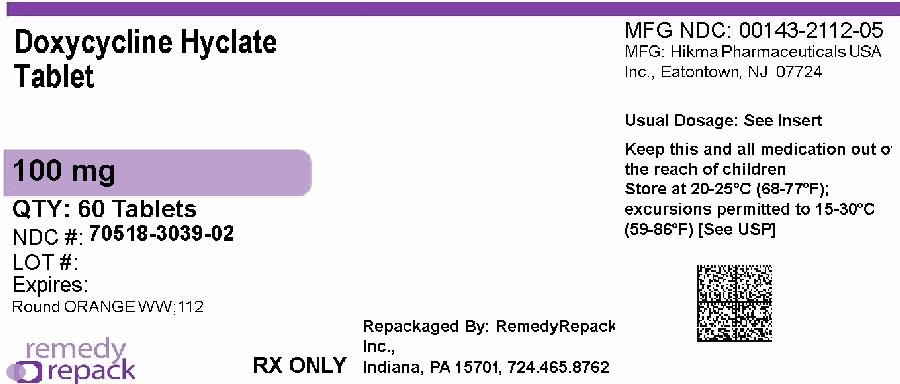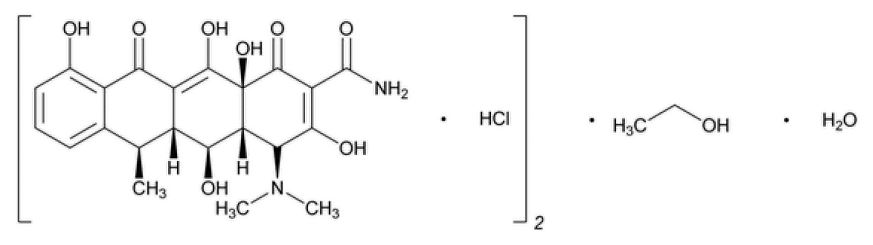 DRUG LABEL: Doxycycline
NDC: 70518-3039 | Form: TABLET, COATED
Manufacturer: REMEDYREPACK INC.
Category: prescription | Type: HUMAN PRESCRIPTION DRUG LABEL
Date: 20260217

ACTIVE INGREDIENTS: DOXYCYCLINE HYCLATE 100 mg/1 1
INACTIVE INGREDIENTS: SILICON DIOXIDE; STARCH, CORN; CROSCARMELLOSE SODIUM; DOCUSATE SODIUM; SODIUM BENZOATE; MAGNESIUM STEARATE; MICROCRYSTALLINE CELLULOSE; FD&C BLUE NO. 2; FD&C YELLOW NO. 6; HYPROMELLOSE, UNSPECIFIED; POLYETHYLENE GLYCOL, UNSPECIFIED; TITANIUM DIOXIDE

DOXYCYCLINE HYCLATE TABLETS, USP
Rx only

To reduce the development of drug-resistant bacteria and maintain the effectiveness of Doxycycline Hyclate Tablets and other antibacterial drugs, Doxycycline Hyclate Tablets should be used only to treat or prevent infections that are proven or strongly suspected to be caused by bacteria.

DESCRIPTION

Doxycycline Hyclate Tablets, USP is an antibacterial drug synthetically derived from oxytetracycline. The structural formula of doxycycline hyclate is:

with a molecular formula of (C22H24N2O8•HCL)2•C2H6O•H2Oand a molecular weight of 1025.88.

The chemical designation for doxycycline is 2-Naphthacenecarboxamide, 4-(dimethylamino)-1, 4, 4a, 5, 5a, 6, -11, 12a-octahydro-3,5,10, 12, 12a-pentahydroxy-6-methyl-1, 11-dioxo-monohydrochloride, compound with ethanol(2:1), monohydrate, [4s-(4α, 4aα, 5α, 5aα, 6α, 12aα)].

Doxycycline is a yellow crystalline powder. Doxycycline hyclate is soluble in water. Doxycycline has a high degree of lipoid solubility and a low affinity for calcium binding. It is highly stable in normal human serum. Doxycycline will not degrade into an epianhydro form.

Each tablet for oral administration contains doxycycline hyclate equivalent to 100 mg of doxycycline (anhydrous). Inactive ingredients are: Colloidal Silicon Dioxide, Corn Starch, Croscarmellose Sodium, Docusate Sodium, Sodium Benzoate, Magnesium Stearate, and Microcrystalline Cellulose. Film Coating and Polishing contains: FD&C Blue No. 2, FD&C Yellow No. 6, Hydroxypropyl Methylcellulose, Polyethylene Glycol, and Titanium Dioxide.

CLINICAL PHARMACOLOGY

Tetracyclines are readily absorbed and are bound to plasma proteins in varying degree. They are concentrated by the liver in the bile, and excreted in the urine and feces at high concentrations and in a biologically active form. Doxycycline is virtually completely absorbed after oral administration.

Following a 200 mg dose, normal adult volunteers averaged peak serum levels of 2.6 mcg/mL of doxycycline at 2 hours, decreasing to 1.45 mcg/mL at 24 hours. Excretion of doxycycline by the kidney is about 40% per 72 hours in individuals with normal function (creatinine clearance about 75 mL/min.). This percentage excretion may fall as low as 1 to 5% per 72 hours in individuals with severe renal insufficiency (creatinine clearance below 10 mL/min.). Studies have shown no significant difference in serum half-life of doxycycline (range 18 to 22 hours) in individuals with normal and severely impaired renal function.

Hemodialysis does not alter serum half-life.

Results of animal studies indicate that tetracyclines cross the placenta and are found in fetal tissues.

Population pharmacokinetic analysis of sparse concentration-time data of doxycycline following standard of care intravenous and oral dosing in 44 pediatric patients (2-18 years of age) showed that allometrically -scaled clearance (CL) of doxycycline in pediatric patients ≥2 to ≤8 years of age (median [range] 3.58 [2.27-10.82] L/h/70 kg, N =11) did not differ significantly from pediatric patients >8 to 18 years of age
(3.27 [1.11-8.12] L/h/70 kg, N=33). For pediatric patients weighing ≤45 kg, body weight normalized doxycycline CL in those ≥2 to ≤8 years of age (median [range] 0.071 [0 .041-0.202] L/kg/h, N=10) did not differ significantly from those >8 to 18 years of age (0.081 [0.035-0.126] L/kg/h, N=8). In pediatric patients weighing >45 kg, no clinically significant differences in body weight normalized doxycycline CL were observed between those ≥2 to ≤8 years (0.050 L/kg/h, N=l) and those >8 to 18 years of age (0.044 [0.014-0.121] L/kg/h, N=25). No clinically significant difference in CL between oral and IV dosing was observed in the small cohort of pediatric patients who received the oral (N=19) or IV (N=2l) formulation alone.

Microbiology

Mechanism of Action

Doxycycline inhibits bacterial protein synthesis by binding to the 30S ribosomal subunit. Doxycycline has bacteriostatic activity against a broad range of Gram-positive and Gram-negative bacteria.

Resistance

Cross resistance with other tetracyclines is common.

Antimicrobial Activity

Doxycycline has been shown to be active against most isolates of the following microorganisms, both in vitroand in clinical infections as described in the INDICATIONS AND USAGEsection of the package insert for Doxycycline Hyclate Tablets.

Gram-Negative Bacteria

Acinetobacterspecies

Bartonella bacilliformis

Brucellaspecies

Klebsiellaspecies

Klebsiella granulomatis

Campylobacter fetus

Enterobacter aerogenes

Escherichia coli

Francisella tularensis

Haemophilus ducreyi

Haemophilus influenzae

Neisseria gonorrhoeae

Shigellaspecies

Vibrio cholerae

Yersinia pestis

Gram-Positive Bacteria

Bacillus anthracis

Listeria monocytogenes

Streptococcus pneumoniae

Anaerobic Bacteria

Clostridiumspecies

Fusobacterium fusiforme

Propionibacterium acnes

Other Bacteria

Nocardiaeand other aerobic Actinomycesspecies

Borrelia recurrentis

Chlamydophila psittaci

Chlamydia trachomatis

Mycoplasma pneumoniae

Rickettsiae

Treponema pallidum

Treponema pallidumsubspecies pertenue

Ureaplasma urealyticum

Parasites

Balantidium coli

Entamoebaspecies

Plasmodium falciparum*

*Doxycycline has been found to be active against the asexual erythrocytic forms of Plasmodium falciparum,but not against the gametocytes of P. falciparum. The precise mechanism of action of the drug is not known.

Susceptibility Testing

For specific information regarding susceptibility test interpretive criteria and associated test methods and quality control standards recognized by FDA for this drug, please see: https://www.fda.gov/STIC.

INDICATIONS AND USAGE

To reduce the development of drug-resistant bacteria and maintain effectiveness of Doxycycline Hyclate Tablets and other antibacterial drugs, Doxycycline Hyclate Tablets should be used only to treat or prevent infections that are proven or strongly suspected to be caused by susceptible bacteria. When culture and susceptibility information are available, they should be considered in selecting or modifying antibacterial therapy. In the absence of such data, local epidemiology and susceptibility patterns may contribute to the empiric selection of therapy.

Treatment

Doxycycline is indicated for the treatment of the following infections:

- Rocky Mountain spotted fever, typhus fever and the typhus group, Q fever, rickettsialpox, and tick fevers caused by Rickettsiae .
- Respiratory tract infections caused by Mycoplasma pneumoniae.
- Lymphogranuloma venereum caused by Chlamydia trachomatis.
- Psittacosis (ornithosis) caused by Chlamydophila psittaci.
- Trachoma caused by Chlamydia trachomatis, although the infectious agent is not always eliminated, as judged by immunofluorescence.
- Inclusion conjunctivitis caused by Chlamydia trachomatis.
- Uncomplicated urethral, endocervical, or rectal infections in adults caused by Chlamydia trachomatis.
- Nongonococcal urethritis caused by Ureaplasma urealyticum.
- Relapsing fever due to Borrelia recurrentis.

Doxycycline is also indicated for the treatment of infections caused by the following gram-negative microorganisms:

- Chancroid caused by Haemophilus ducreyi.
- Plague due to Yersinia pestis.
- Tularemia due to Francisella tularensis.
- Cholera caused by Vibrio cholerae.
- Campylobacter fetus infections caused by Campylobacter fetus.
- Brucellosis due to Brucellaspecies (in conjunction with streptomycin).
- Bartonellosis due to Bartonella bacilliformis.
- Granuloma inguinale caused by Klebsiella granulomatis.

Because many strains of the following groups of microorganisms have been shown to be resistant to doxycycline, culture and susceptibility testing are recommended.

Doxycycline is indicated for treatment of infections caused by the following gram-negative bacteria, when bacteriologic testing indicates appropriate susceptibility to the drug:

- Escherichia coli.
- Enterobacter aerogenes.
- Shigellaspecies.
- Acinetobacterspecies.
- Respiratory tract infections caused by Haemophilus influenzae.
- Respiratory tract and urinary tract infections caused by Klebsiellaspecies.

Doxycycline is indicated for treatment of infections caused by the following gram-positive microorganisms when bacteriologic testing indicates appropriate susceptibility to the drug:

- Upper respiratory infections caused by Streptococcus pneumoniae.
- Anthrax due to Bacillus anthracis, including inhalational anthrax (post-exposure): to reduce the incidence or progression of disease following exposure to aerosolized Bacillus anthracis.

When penicillin is contraindicated, doxycycline is an alternative drug in the treatment of the following infections:

- Uncomplicated gonorrhea caused by Neisseria gonorrhoeae.
- Syphilis caused by Treponema pallidum.
- Yaws caused by Treponema pallidumsubspecies pertenue.
- Listeriosis due to Listeria monocytogenes.
- Vincent’s infection caused by Fusobacterium fusiforme.
- Actinomycosis caused by Actinomyces israelii.
- Infections caused by Clostridiumspecies.

In acute intestinal amebiasis, doxycycline may be a useful adjunct to amebicides.

In severe acne, doxycycline may be useful adjunctive therapy.

Prophylaxis

Doxycycline is indicated for the prophylaxis of malaria due to Plasmodium falciparumin short-term travelers (<4 months) to areas with chloroquine and/or pyrimethamine-sulfadoxine resistant strains (See DOSAGE AND ADMINISTRATION section and Information for Patients subsection of the PRECAUTIONSsection).

CONTRAINDICATIONS

This drug is contraindicated in persons who have shown hypersensitivity to any of the tetracyclines.

WARNINGS

The use of drugs of the tetracycline class during tooth development (last half of pregnancy, infancy and childhood to the age of 8 years) may cause permanent discoloration of the teeth (yellow-gray-brown). This adverse reaction is more common during long-term use of the drugs, but it has been observed following repeated short-term courses. Enamel hypoplasia has also been reported. Use doxycycline in pediatric patients 8 years of age or less only when the potential benefits are expected to outweigh the risks in severe or life-threatening conditions (e.g., anthrax, Rocky Mountain spotted fever), particularly when there are no alternative therapies.

Clostridioides difficileassociated diarrhea (CDAD) has been reported with use of nearly all antibacterial agents, including Doxycycline Hyclate Tablets, and may range in severity from mild diarrhea to fatal colitis. Treatment with antibacterial agents alters the normal flora of the colon leading to overgrowth of C. difficile.

C. difficileproduces toxins A and B which contribute to the development of CDAD. Hypertoxin producing strains of C. difficilecause increased morbidity and mortality, as these infections can be refractory to antimicrobial therapy and may require colectomy. CDAD must be considered in all patients who present with diarrhea following the use of antibacterial drugs. Careful medical history is necessary since CDAD has been reported to occur over two months after the administration of antibacterial agents.

If CDAD is suspected or confirmed, ongoing use of antibacterial drugs not directed against C. difficilemay need to be discontinued. Appropriate fluid and electrolyte management, protein supplementation, antibacterial treatment of C. difficile, and surgical evaluation should be instituted as clinically indicated.

Severe skin reactions, such as exfoliative dermatitis, erythema multiforme, Stevens-Johnson syndrome, toxic epidermal necrolysis, and drug reaction with eosinophilia and systemic symptoms (DRESS) have been reported in patients receiving doxycycline. Fixed drug eruptions have occurred with doxycycline and have been associated with worsening severity upon subsequent administrations, including generalized bullous fixed drug eruption (See ADVERSE REACTIONS). If severe skin reactions occur, discontinue Doxycycline Hyclate Tablets immediately and institute appropriate therapy.

Intracranial hypertension (IH, pseudotumor cerebri) has been associated with the use of tetracyclines including Doxycycline Hyclate Tablets. Clinical manifestations of IH include headache, blurred vision, diplopia, and vision loss; papilledema can be found on fundoscopy. Women of childbearing age who are overweight or have a history of IH are at greater risk for developing tetracycline associated IH. Concomitant use of isotretinoin and Doxycycline Hyclate Tablets should be avoided because isotretinoin is also known to cause pseudotumor cerebri.

Although IH typically resolves after discontinuation of treatment, the possibility for permanent visual loss exists. If visual disturbance occurs during treatment, prompt ophthalmologic evaluation is warranted. Since intracranial pressure can remain elevated for weeks after drug cessation patients should be monitored until they stabilize.

All tetracyclines form a stable calcium complex in any bone-forming tissue. A decrease in fibula growth rate has been observed in prematures given oral tetracycline in doses of 25 mg/kg every 6 hours. This reaction was shown to be reversible when the drug was discontinued.

Results of animal studies indicate that tetracyclines cross the placenta, are found in fetal tissues, and can have toxic effects on the developing fetus (often related to retardation of skeletal development). Evidence of embryotoxicity has also been noted in animals treated early in pregnancy. If any tetracycline is used during pregnancy or if the patient becomes pregnant while taking this drug, the patient should be apprised of the potential hazard to the fetus.

The antianabolic action of the tetracyclines may cause an increase in BUN. Studies to date indicate that this does not occur with the use of doxycycline in patients with impaired renal function.

Photosensitivity manifested by an exaggerated sunburn reaction has been observed in some individuals taking tetracyclines. Patients apt to be exposed to direct sunlight or ultraviolet light should be advised that this reaction can occur with tetracycline drugs, and treatment should be discontinued at the first evidence of skin erythema.

PRECAUTIONS

General

As with other antibacterial drugs, use of Doxycycline Hyclate Tablets may result in overgrowth of nonsusceptible organisms, including fungi. If superinfection occurs, Doxycycline Hyclate Tablets should be discontinued and appropriate therapy instituted.

Incision and drainage or other surgical procedures should be performed in conjunction with antibacterial therapy, when indicated.

Doxycycline offers substantial but not complete suppression of the asexual blood stages of Plasmodiumstrains.

Doxycycline does not suppress P. falciparum’s sexual blood stage gametocytes. Subjects completing this prophylactic regimen may still transmit the infection to mosquitoes outside endemic areas.

Prescribing Doxycycline Hyclate Tablets in the absence of proven or strongly suspected bacterial infection or a prophylactic indication is unlikely to provide benefit to the patient and increases the risk of the development of drug-resistant bacteria.

Information for Patients

Patients taking doxycycline for malaria prophylaxis should be advised:

- that no present-day antimalarial agent, including doxycycline, guarantees protection against malaria.
- to avoid being bitten by mosquitoes by using personal protective measures that help avoid contact with mosquitoes, especially from dusk to dawn (e.g., staying in well-screened areas, using mosquito nets, covering the body with clothing, and using an effective insect repellent).
- that doxycycline prophylaxis:
- should begin 1 to 2 days before travel to the malarious area,
- should be continued daily while in the malarious area and after leaving the malarious area,
- should be continued for 4 further weeks to avoid development of malaria after returning from an endemic area,
- should not exceed 4 months.

All patients taking doxycycline should be advised:

- to avoid excessive sunlight or artificial ultraviolet light while receiving doxycycline and to discontinue therapy if phototoxicity (e.g., skin eruption, etc.) occurs. Sunscreen or sunblock should be considered (See WARNINGS).
- to drink fluids liberally along with doxycycline to reduce the risk of esophageal irritation and ulceration (See ADVERSE REACTIONS).
- that the absorption of tetracyclines is reduced when taken with foods, especially those which contain calcium. However, the absorption of doxycycline is not markedly influenced by simultaneous ingestion of food or milk (See Drug Interactions).
- that the absorption of tetracyclines is reduced when taking bismuth subsalicylate (See Drug Interactions).
- that the use of doxycycline might increase the incidence of vaginal candidiasis.

Patients should be counseled that antibacterial drugs, including Doxycycline Hyclate Tablets should only be used to treat bacterial infections. They do not treat viral infections (e.g., the common cold). When Doxycycline Hyclate Tablets are prescribed to treat a bacterial infection, patients should be told that although it is common to feel better early in the course of therapy, the medication should be taken exactly as directed. Skipping doses or not completing the full course of therapy may (1) decrease the effectiveness of the immediate treatment and (2) increase the likelihood that bacteria will develop resistance and will not be treatable by Doxycycline Hyclate Tablets or other antibacterial drugs in the future.

Diarrhea is a common problem caused by antibacterial drugs, which usually ends when the antibacterials are discontinued. Sometimes after starting treatment with antibacterial drugs, patients can develop watery and bloody stools (with or without stomach cramps and fever) even as late as two or more months after having taken the last dose of the antibacterial drug. If this occurs, patients should contact their physician as soon as possible.

Repackaged By / Distributed By: RemedyRepack Inc.

625 Kolter Drive, Indiana, PA 15701

(724) 465-8762

Laboratory Tests

In venereal disease, when co-existent syphilis is suspected, dark field examinations should be done before treatment is started and the blood serology repeated monthly for at least 4 months.

In long-term therapy, periodic laboratory evaluation of organ systems, including hematopoietic, renal, and hepatic studies, should be performed.

Drug Interactions

Because tetracyclines have been shown to depress plasma prothrombin activity, patients who are on anticoagulant therapy may require downward adjustment of their anticoagulant dosage.

Since bacteriostatic drugs may interfere with the bactericidal action of penicillin, it is advisable to avoid giving tetracyclines in conjunction with penicillin.

Absorption of tetracyclines is impaired by antacids containing aluminum, calcium, or magnesium, and iron-containing preparations.

Absorption of tetracyclines is impaired by bismuth subsalicylate.

Barbiturates, carbamazepine, phenytoin, and rifampin shorten the half-life of doxycycline, thereby lowering doxycycline concentration in the body.

Concurrent use of tetracycline may render oral contraceptives less effective.

Drug/Laboratory Test Interactions

False elevations of urinary catecholamine levels may occur due to interference with the fluorescence test.

Carcinogenesis, Mutagenesis, Impairment of Fertility

Long-term studies in animals to evaluate carcinogenic potential of doxycycline have not been conducted. However, there has been evidence of oncogenic activity in rats in studies with the related antibacterial drugs, oxytetracycline (adrenal and pituitary tumors), and minocycline (thyroid tumors).

Likewise, although mutagenicity studies of doxycycline have not been conducted, positive results in in vitromammalian cell assays have been reported for related antibacterial drugs (tetracycline, oxytetracycline).

Doxycycline administered orally at dosage levels as high as 250 mg/kg/day had no apparent effect on the fertility of female rats. Effect on male fertility has not been studied.

Pregnancy

Teratogenic Effects

There are no adequate and well-controlled studies on the use of doxycycline in pregnant women. The vast majority of reported experience with doxycycline during human pregnancy is short-term, first trimester exposure. There are no human data available to assess the effects of long-term therapy of doxycycline in pregnant women, such as that proposed for treatment of anthrax exposure. An expert review of published data on experiences with doxycycline use during pregnancy by TERIS – the Teratogen Information System – concluded that therapeutic doses during pregnancy are unlikely to pose a substantial teratogenic risk (the quantity and quality of data were assessed as limited to fair), but the data are insufficient to state that there is no risk.^1A case-control study (18,515 mothers of infants with congenital anomalies and 32,804 mothers of infants with no congenital anomalies) shows a weak but marginally statistically significant association with total malformations and use of doxycycline anytime during pregnancy. Sixty-three (0.19%) of the controls and fifty-six (0.30%) of the cases were treated with doxycycline. This association was not seen when the analysis was confined to maternal treatment during the period of organogenesis (i.e., in the second and third months of gestation) with the exception of a marginal relationship with neural tube defect based on only two exposed cases.^2

A small prospective study of 81 pregnancies describes 43 pregnant women treated for 10 days with doxycycline during early first trimester. All mothers reported their exposed infants were normal at 1 year of age.^3

Nonteratogenic Effects

(See WARNINGS.)

Labor and Delivery

The effect of tetracyclines on labor and delivery is unknown.

Nursing Mothers

Tetracyclines are excreted in human milk; however, the extent of absorption of tetracyclines, including doxycycline, by the breastfed infant is not known. Short-term use by lactating women is not necessarily contraindicated; however, the effects of prolonged exposure to doxycycline in breast milk are unknown.^4Because of the potential for serious adverse reactions in nursing infants from doxycycline, a decision should be made whether to discontinue nursing or to discontinue the drug, taking into account the importance of the drug to the mother (See WARNINGS).

Pediatric Use

Because of the effects of drugs of the tetracycline class on tooth development and growth, use doxycycline in pediatric patients 8 years of age or less only when the potential benefits are expected to outweigh the risks in severe or life-threatening conditions (e.g., anthrax, Rocky Mountain spotted fever), particularly when there are no alternative therapies (See WARNINGSand DOSAGE AND ADMINISTRATION).

ADVERSE REACTIONS

Due to oral doxycycline’s virtually complete absorption, side effects of the lower bowel, particularly diarrhea, have been infrequent. The following adverse reactions have been observed in patients receiving tetracyclines:

Gastrointestinal: anorexia, nausea, vomiting, diarrhea, glossitis, dysphagia, enterocolitis, inflammatory lesions (with monilial overgrowth) in the anogenital region, and pancreatitis. Hepatotoxicity has been reported rarely. These reactions have been caused by both the oral and parenteral administration of tetracyclines. Superficial discoloration of the adult permanent dentition, reversible upon drug discontinuation and professional dental cleaning has been reported. Permanent tooth discoloration and enamel hypoplasia may occur with drugs of the tetracycline class when used during tooth development (See WARNINGS). Rare instances of esophagitis and esophageal ulcerations have been reported in patients receiving capsule and tablet forms of the drugs in the tetracycline class. Most of these patients took medications immediately before going to bed (See DOSAGE AND ADMINISTRATION).

Skin: toxic epidermal necrolysis, Stevens-Johnson syndrome, erythema multiforme, fixed drug eruption, skin hyperpigmentation, maculopapular and erythematous rashes. Exfoliative dermatitis has been reported but is uncommon. Photosensitivity is discussed above (See WARNINGS).

Renal toxicity: Rise in BUN has been reported and is apparently dose related (See WARNINGS).

Immune: Hypersensitivity reactions including urticaria, angioneurotic edema, anaphylaxis, anaphylactoid purpura, serum sickness, pericarditis, exacerbation of systemic lupus erythematosus, drug reaction with eosinophilia and systemic symptoms (DRESS), and Jarisch-Herxheimer reaction has been reported in the setting of spirochete infections treated with doxycycline.

Blood: Hemolytic anemia, thrombocytopenia, neutropenia, and eosinophilia have been reported.

Psychiatric: Depression, anxiety, suicidal ideation, insomnia, abnormal dreams, hallucination.

Other: Bulging fontanels in infants and intracranial hypertension in adults (See WARNINGS).

When given over prolonged periods, tetracyclines have been reported to produce brown-black microscopic discoloration of the thyroid gland. No abnormalities of thyroid function studies are known to occur.

To report SUSPECTED ADVERSE REACTIONS, contact Hikma Pharmaceuticals USA Inc. at
1-800-962-8364, or FDA at 1-800-FDA-1088 or www.fda.gov/medwatch.

OVERDOSAGE

In case of overdosage, discontinue medication, treat symptomatically and institute supportive measures. Dialysis does not alter serum half-life and thus would not be of benefit in treating cases of overdosage.

DOSAGE AND ADMINISTRATION

The usual dosage and frequency of administration of doxycycline differs from that of the other tetracyclines. Exceeding the recommended dosage may result in an increased incidence of side effects.

Adults

The usual dose of oral doxycycline is 200 mg on the first day of treatment (administered 100 mg every 12 hours) followed by a maintenance dose of 100 mg/day. In the management of more severe infections (particularly chronic infections of the urinary tract), 100 mg every 12 hours is recommended.

Pediatric Patients

For all pediatric patients weighing less than 45 kg with severe or life-threatening infections (e.g., anthrax, Rocky Mountain spotted fever), the recommended dosage is 2.2 mg/kg of body weight administered every 12 hours. Children weighing 45 kg or more should receive the adult dose (See WARNINGSand PRECAUTIONS).

For pediatric patients with less severe disease (greater than 8 years of age and weighing less than 45 kg), the recommended dosage schedule is 4.4 mg/kg of body weight divided into two doses on the first day of treatment, followed by a maintenance dose of 2.2 mg/kg of body weight (given as a single daily dose or divided into twice daily doses). For pediatric patients weighing over 45 kg, the usual adult dose should be used.

The therapeutic antibacterial serum activity will usually persist for 24 hours following recommended dosage.

When used in streptococcal infections, therapy should be continued for 10 days.

Administration of adequate amounts of fluid along with capsule and tablet forms of drugs in the tetracycline class is recommended to wash down the drugs and reduce the risk of esophageal irritation and ulceration (See ADVERSE REACTIONS).

If gastric irritation occurs, it is recommended that doxycycline be given with food or milk. The absorption of doxycycline is not markedly influenced by simultaneous ingestion of food or milk.

Studies to date have indicated that administration of doxycycline at the usual recommended doses does not lead to excessive accumulation of doxycycline in patients with renal impairment.

Uncomplicated gonococcal infections in adults (except anorectal infections in men): 100 mg, by mouth, twice a day for 7 days. As an alternate single visit dose, administer 300 mg stat followed in one hour by a second 300 mg dose. The dose may be administered with food, including milk or carbonated beverage, as required.

Uncomplicated urethral, endocervical, or rectal infection in adults caused by Chlamydia trachomatis:
100 mg, by mouth twice a day for 7 days.

Nongonococcal urethritis (NGU) caused by C. trachomatisor U. urealyticum:100 mg by mouth, twice a day for 7 days.

Syphilis – early: Patients who are allergic to penicillin should be treated with doxycycline 100 mg, by mouth, twice a day for 2 weeks.

Syphilis of more than one year’s duration: Patients who are allergic to penicillin should be treated with doxycycline 100 mg, by mouth, twice a day for 4 weeks.

Acute epididymo-orchitis caused by N. gonorrhoeae:100 mg, by mouth, twice a day for at least 10 days.

Acute epididymo-orchitis caused by C. trachomatis:100 mg, by mouth, twice a day for at least 10 days.

For prophylaxis of malaria: For adults, the recommended dose is 100 mg daily. For children over 8 years of age, the recommended dose is 2 mg/kg given once daily up to the adult dose. Prophylaxis should begin 1 to 2 days before travel to the malarious area. Prophylaxis should be continued daily during travel in the malarious area and for 4 weeks after the traveler leaves the malarious area.

Inhalational anthrax (post-exposure):

ADULTS: 100 mg of doxycycline, by mouth, twice a day for 60 days.

CHILDREN: weighing less than 45 kg; 2.2 mg/kg of body weight by mouth, twice a day for 60 days. Children weighing 45 kg or more should receive the adult dose.

HOW SUPPLIED

Doxycycline Hyclate Tablets, USP equivalent to 100 mg doxycycline: Orange Coated, Round, Unscored Tablets, Debossed “WW 112”.

NDC: 70518-3039-00

NDC: 70518-3039-01

NDC: 70518-3039-02

NDC: 70518-3039-03

NDC: 70518-3039-04

NDC: 70518-3039-05

NDC: 70518-3039-06

NDC: 70518-3039-07

PACKAGING: 14 in 1 BOTTLE PLASTIC

PACKAGING: 14 in 1 BOTTLE PLASTIC

PACKAGING: 60 in 1 BOTTLE PLASTIC

PACKAGING: 2 in 1 BOX

PACKAGING: 1 in 1 POUCH

PACKAGING: 2 in 1 BOTTLE PLASTIC

PACKAGING: 20 in 1 BOTTLE PLASTIC

PACKAGING: 20 in 1 BOTTLE PLASTIC

Store at 20° to 25°C (68° to 77°F), [See USP Controlled Room Temperature]. Protect from light and moisture.

Dispense in a tight, light-resistant container as defined in the USP using a child-resistant closure.

Repackaged and Distributed By:

Remedy Repack, Inc.

625 Kolter Dr. Suite #4 Indiana, PA 1-724-465-8762

ANIMAL PHARMACOLOGY AND ANIMAL TOXICOLOGY

Hyperpigmentation of the thyroid has been produced by members of the tetracycline class in the following species: in rats by oxytetracycline, doxycycline, tetracycline PO4, and methacycline; in minipigs by doxycycline, minocycline, tetracycline PO4, and methacycline; in dogs by doxycycline and minocycline; in monkeys by minocycline.

Minocycline, tetracycline PO4, methacycline, doxycycline, tetracycline base, oxytetracycline HCl, and tetracycline HCl were goitrogenic in rats fed a low iodine diet. This goitrogenic effect was accompanied by high radioactive iodine uptake. Administration of minocycline also produced a large goiter with high radioiodine uptake in rats fed a relatively high iodine diet.

Treatment of various animal species with this class of drugs has also resulted in the induction of thyroid hyperplasia in the following: in rats and dogs (minocycline); in chickens (chlortetracycline); and in rats and mice (oxytetracycline). Adrenal gland hyperplasia has been observed in goats and rats treated with oxytetracycline.

REFERENCES

1. 1.Friedman JM and Polifka JE. Teratogenic Effects of Drugs. A Resource for Clinicians (TERIS).Baltimore, MD: The Johns Hopkins University Press, 2000: 149–195.
2. 2. Cziezel AE and Rockenbauer M. Teratogenic study of doxycycline. Obstet Gynecol1997; 89: 524–528.
3. 3. Horne HW Jr and Kundsin RB. The role of mycoplasma among 81 consecutive pregnancies: a prospective study. Int J Fertil1980; 25: 315–317.
4. 4. Hale T. Medications and Mothers Milk.9thedition. Amarillo, TX: Pharmasoft Publishing, 2000: 225–226.

Repackaged and Distributed By:
Remedy Repack, Inc.
625 Kolter Dr. Suite #4 Indiana, PA 1-724-465-8762

PACKAGE LABEL

DRUG: Doxycycline Hyclate

GENERIC: Doxycycline Hyclate

DOSAGE: TABLET, COATED

ADMINSTRATION: ORAL

NDC: 70518-3039-0

NDC: 70518-3039-1

NDC: 70518-3039-2

NDC: 70518-3039-3

NDC: 70518-3039-4

NDC: 70518-3039-5

NDC: 70518-3039-6

NDC: 70518-3039-7

COLOR: orange

SHAPE: ROUND

SCORE: No score

SIZE: 17 mm

IMPRINT: WW;112

PACKAGING: 14 in 1 BOTTLE PLASTIC

PACKAGING: 14 in 1 BOTTLE PLASTIC

PACKAGING: 60 in 1 BOTTLE PLASTIC

PACKAGING: 2 in 1 BOX

PACKAGING: 1 in 1 POUCH

PACKAGING: 2 in 1 BOTTLE PLASTIC

PACKAGING: 20 in 1 BOTTLE PLASTIC

PACKAGING: 20 in 1 BOTTLE PLASTIC

ACTIVE INGREDIENT(S):

- DOXYCYCLINE HYCLATE 100mg in 1

INACTIVE INGREDIENT(S):

- SILICON DIOXIDE
- STARCH, CORN
- CROSCARMELLOSE SODIUM
- DOCUSATE SODIUM
- SODIUM BENZOATE
- MAGNESIUM STEARATE
- MICROCRYSTALLINE CELLULOSE
- FD&C BLUE NO. 2
- FD&C YELLOW NO. 6
- HYPROMELLOSE, UNSPECIFIED
- POLYETHYLENE GLYCOL, UNSPECIFIED
- TITANIUM DIOXIDE